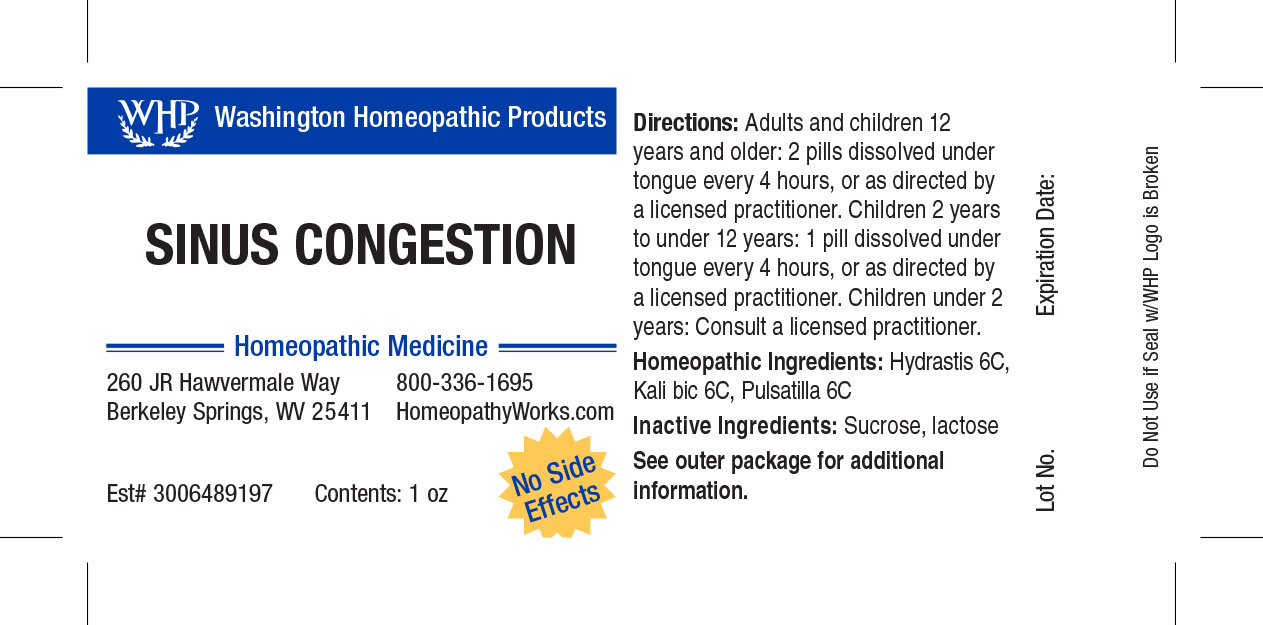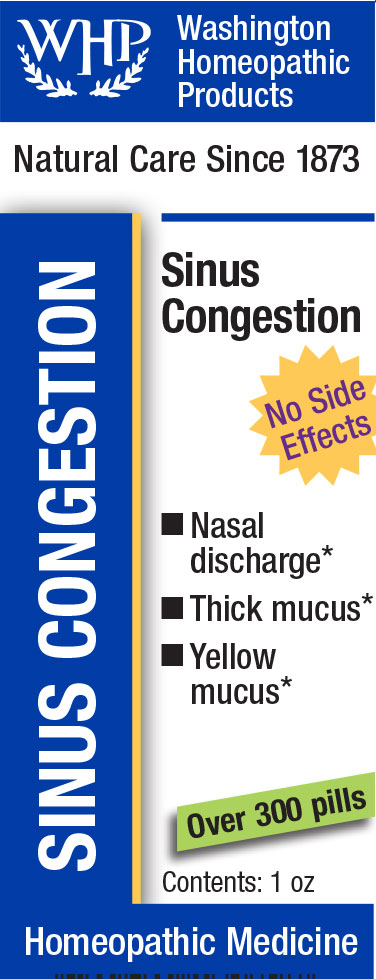 DRUG LABEL: WHP Sinus Congestion
NDC: 71919-802 | Form: PELLET
Manufacturer: Washington Homeopathic Products
Category: homeopathic | Type: HUMAN OTC DRUG LABEL
Date: 20250128

ACTIVE INGREDIENTS: PULSATILLA VULGARIS 6 [hp_C]/1 1; POTASSIUM DICHROMATE 6 [hp_C]/1 1; GOLDENSEAL 6 [hp_C]/1 1
INACTIVE INGREDIENTS: SUCROSE; LACTOSE

WHP Sinus Congestion

ACTIVE INGREDIENTS

HYDRASTIS 6C

KALI BIC 6C

PULSATILLA 6C

USES

Temporarily relieves congested sinuses.

KEEP OUT OF REACH OF CHILDREN

As with all medications, keep out of reach of children.

INDICATIONS

HYDRASTIS Sinuses

KALI BIC Sinuses

PULSATILLA Weeping

STOP USE AND ASK DOCTOR

If symptoms persist or recur, discontinue use. If pregnant or nursing, consult a licensed practitioner before using this product.

DIRECTIONS

Directions: Adults and children 12 years and older: 2 pills dissolved under tongue every 4 hours, or as directed by a licensed practitioner. Children 4 years to under 12 years: 1 pill dissolved under tongue every 4 hours, or as directed by a licensed practitioner. Children under 4 years: Consult a licensed practitioner.

INACTIVE INGREDIENTS

Sucrose/Lactose